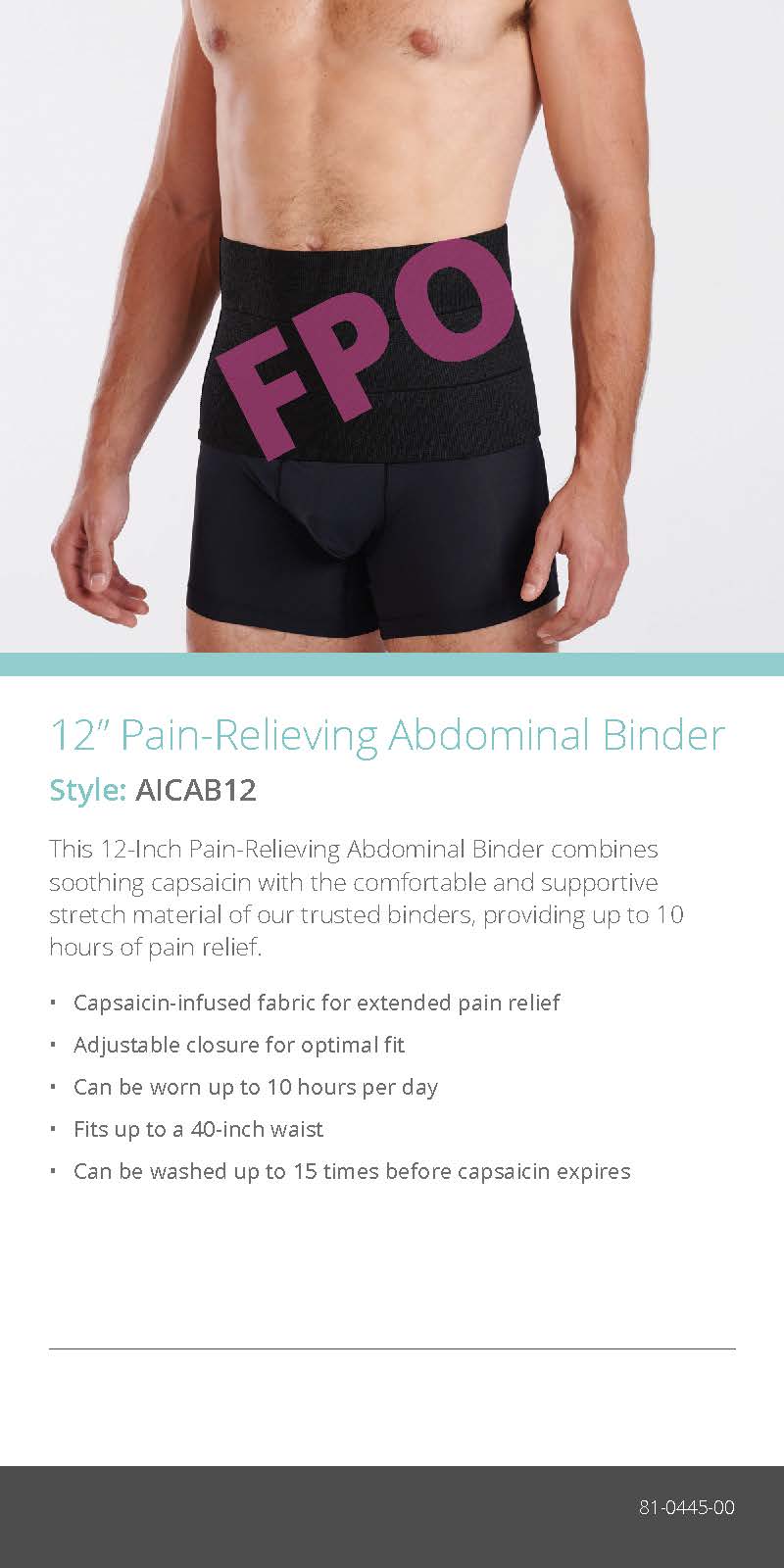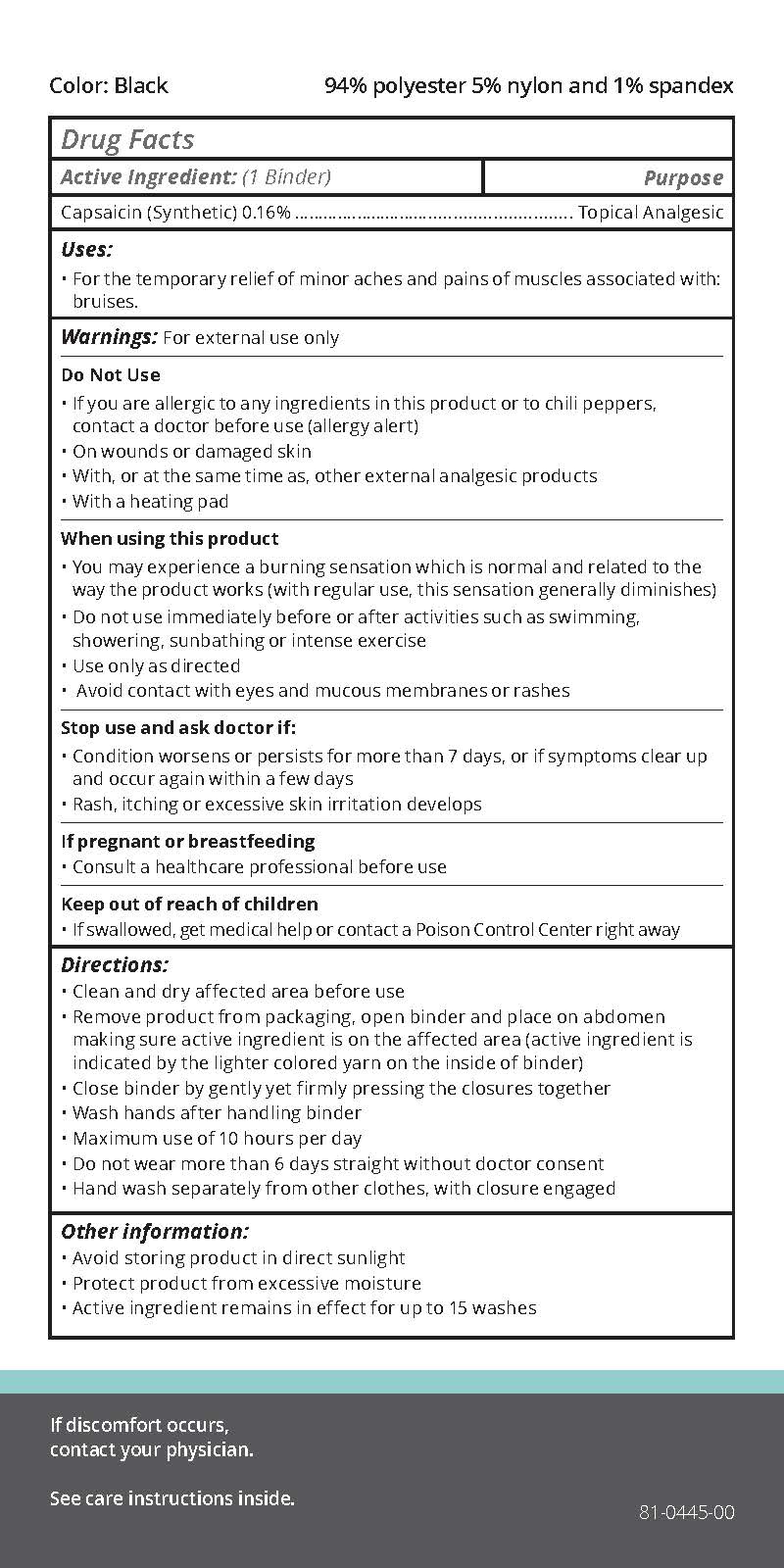 DRUG LABEL: Pain-Relieving Abdominal Binder
NDC: 84721-002 | Form: CLOTH
Manufacturer: The Marena Group LLC
Category: otc | Type: HUMAN OTC DRUG LABEL
Date: 20240913

ACTIVE INGREDIENTS: CAPSAICIN 0.16 g/100 g
INACTIVE INGREDIENTS: BUTYL ACRYLATE/METHYL METHACRYLATE/METHACRYLIC ACID COPOLYMER (18000 MW)

Relieving Abdominal Binder 84721-002-01

Active ingredient

Capsaicin (synthetic) 0.16%

Purpose

Topical Analgesic

Uses

For the temporary relief of minor aches and pains of muscles associated with: bruises.

Warnings

For external use only.

Do not use

- If you are allergic to any ingredients in this product or to chili peppers, contact a doctor before use (allergy alert)
- On wounds or damaged skin
- With, or at the same time as, other external analgesic products
- With a heating pad

When using this product

- You may experience a burning sensation which is normal and related to the way the product works (with regular use, this sensation generally diminishes)
- Do not use immediately before or after activities such as swimming, showering, sunbathing or intense exercise
- Use only as directed
- Avoid contact with eyes and mucous membranes or rashes

Stop use and ask doctor if

- Condition worsens or persists for more than 7 days, or if symptoms clear up and occur again within a few days
- Rash, itching or excessive skin irritation develops

If pregnant or breastfeeding

Consult a healthcare professional before use.

Keep out of reach of children

If swallowed, get medical help or contact a Poison Control Center right away.

Directions

- Clean and dry affected area before use
- Remove product from packaging, open binder and place on abdomen making sure active ingredient is on the affected area (active ingredient is indicated by the lighter colored yarn on the inside of binder)
- Close binder by gently yet firmly pressing the closures together
- Wash hands after handling binder
- Maximum use of 10 hours per day
- Do not wear more than 6 days straight without doctor consent
- Hand wash separately from other clothes, with closure engaged

Other information

- Avoid storing product in direct sunlight
- Protect product from excessive moisture
- Active ingredient remains in effect for up to 15 washes

Inactive ingredient

acrylate copolymer